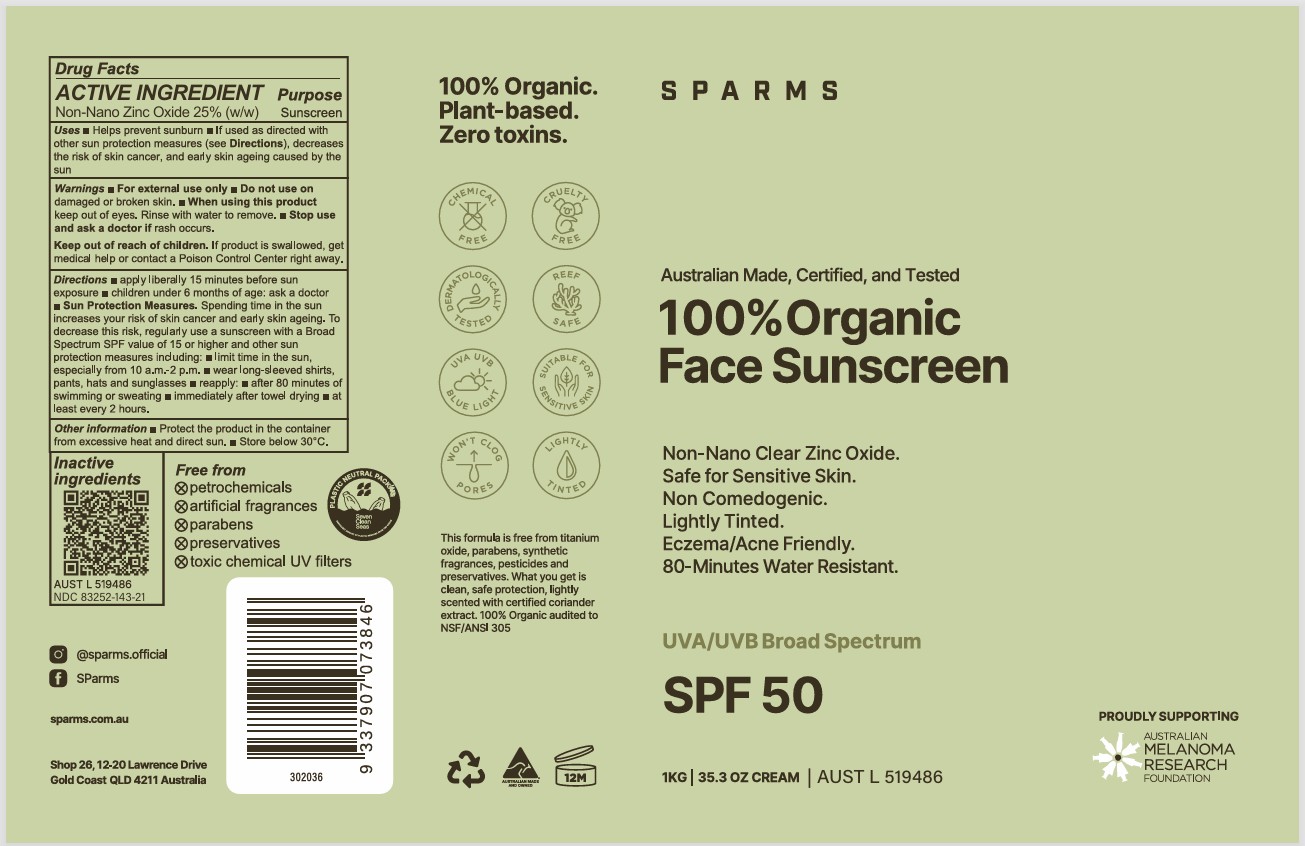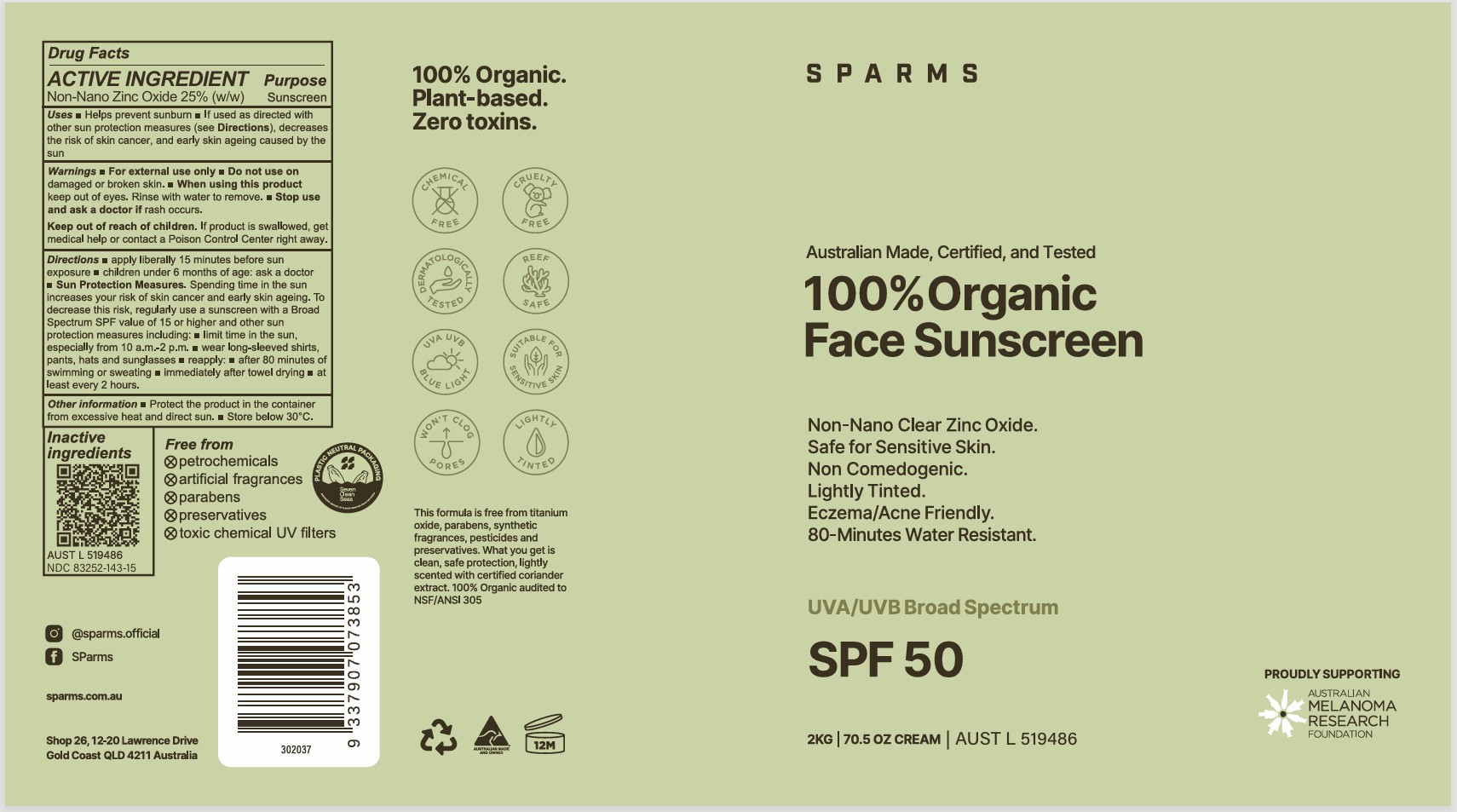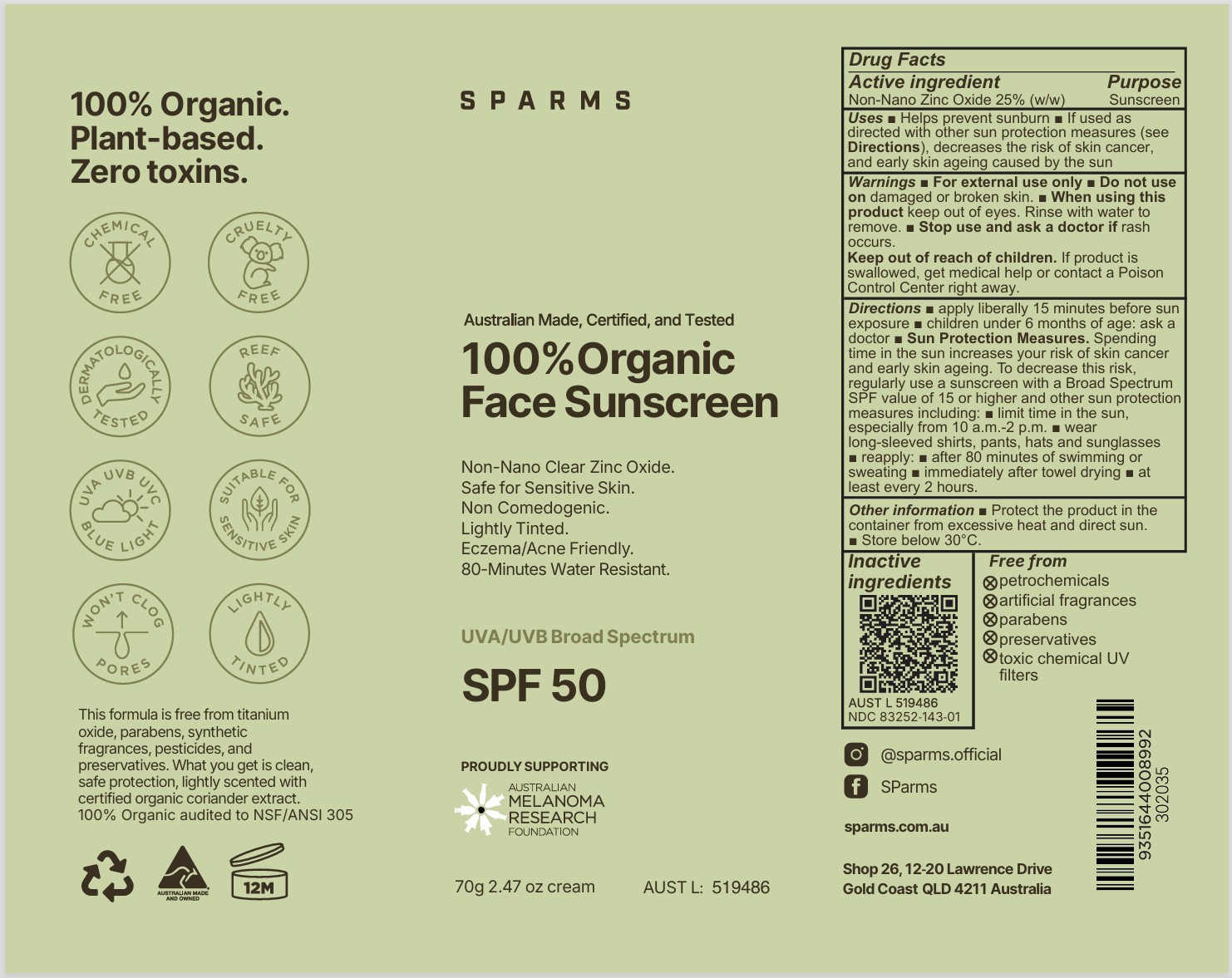 DRUG LABEL: Sparms 100% Organic Face Sunscreen
NDC: 83252-143 | Form: CREAM
Manufacturer: VEGANIC SKN LIMITED
Category: otc | Type: HUMAN OTC DRUG LABEL
Date: 20260215

ACTIVE INGREDIENTS: ZINC OXIDE 25 kg/100 kg
INACTIVE INGREDIENTS: COCONUT ALKANES; PELARGONIUM GRAVEOLENS FLOWER OIL; POMEGRANATE; GLYCERYL STEARATE CITRATE; SODIUM HYALURONATE; SODIUM CHLORIDE; POLYGLYCERYL-3 RICINOLEATE; SODIUM ASCORBATE; XANTHAN GUM; FERRIC OXIDE RED; BISABOLOL; SODIUM HINOKITIOL; FERRIC OXIDE YELLOW; FERROSOFERRIC OXIDE; CORIANDER OIL; KAKADU PLUM; CITRUS PARADISI (GRAPEFRUIT) SEED OIL; HELIANTHUS ANNUUS (SUNFLOWER) SEED OIL; BANANA; HIPPOPHAE RHAMNOIDES SEED OIL; .ALPHA.-TOCOPHEROL ACETATE, D-; WATER; POLYHYDROXYSTEARIC ACID (2300 MW); ISOSTEARIC ACID; CANDELILLA WAX; COCO-CAPRYLATE/CAPRATE; MANDARIN OIL

Sparms 100% Organic Face Sunscreen

ACTIVE INGREDIENT

Zinc oxide - 25%

PURPOSE

Sunscreen

INDICATIONS AND USAGE

kindly refer to label picture

WARNINGS

For external use only.

Do not use on damaged r broken skin.

When using this product keep out of eyes. Rinse with water to remove.
Stop use and ask a doctor if rash occurs.

Keep out of reach of children.

If product is swallowed, get medical help or contact a Poison Control Center right away.

Keep out of reach of children.

DOSAGE AND ADMINISTRATION

Kindly refer to Label

INACTIVE INGREDIENT

See ingredients on label